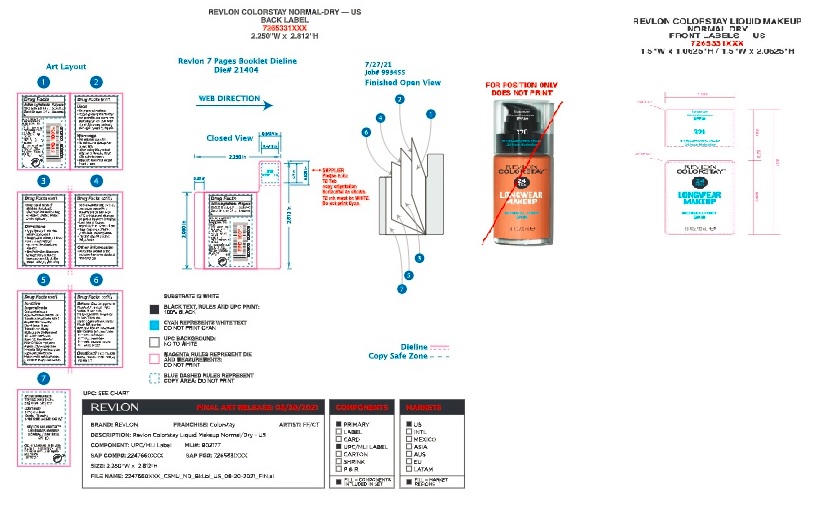 DRUG LABEL: Revlon Colorstay Liquid Makeup for Normal to Dry Skin
NDC: 10967-643 | Form: LIQUID
Manufacturer: Revlon Consumer Products Corp
Category: otc | Type: HUMAN OTC DRUG LABEL
Date: 20241231

ACTIVE INGREDIENTS: ZINC OXIDE 2.1 mg/1 mL; TITANIUM DIOXIDE 4.3 mg/1 mL
INACTIVE INGREDIENTS: WATER; DIMETHICONE; BUTYLENE GLYCOL; PHENYL TRIMETHICONE; METHICONE (20 CST); LAURETH-7; PHENOXYETHANOL; METHYLPARABEN; ETHYLPARABEN; CYCLOMETHICONE 5; TRIMETHYLSILOXYSILICATE (M/Q 0.6-0.8); PEG-9 POLYDIMETHYLSILOXYETHYL DIMETHICONE; TRIBEHENIN; NYLON-12; ALUMINUM OXIDE; MAGNESIUM SULFATE, UNSPECIFIED; SILICON DIOXIDE; HYALURONATE SODIUM; POLYGLYCERYL-3 DIISOSTEARATE; ETHYLENE BRASSYLATE; TRIETHOXYCAPRYLYLSILANE; .ALPHA.-TOCOPHEROL ACETATE; EDETATE SODIUM; LEVOMENOL; ETHYLHEXYL PALMITATE; TOCOPHEROL; SODIUM CITRATE; DIPROPYLENE GLYCOL; SALICYLIC ACID; MALVA SYLVESTRIS FLOWERING TOP; LILIUM CANDIDUM BULB; CYMBIDIUM HOOKERIANUM FLOWER; CAPRYLYL GLYCOL; PEG-12 GLYCERYL DIMYRISTATE; CYCLOMETHICONE 6; POLYSORBATE 20; DISTEARDIMONIUM HECTORITE; TRIETHYL CITRATE; SILICA DIMETHYL SILYLATE

Revlon Colorstay Liquid Makeup for Dry to Normal Skin SPF 20

Active Ingredients:

Titanium Dioxide 4.3 %

Zinc Oxide (nano) 2.1 %

Warnings:

For external use only. Avoid contact with eyes. Discount use if signs of irritation or rash appear. Apply prior to sun exposure

Inactive Ingredients:

Cyclopentasiloxane, Aqua/Water/Eau, Dimethicone, Trimethylsiloxysilicate, PEG-9 Polydimethylsiloxyethyl Dimethicone, Phenyl Trimethicone, Methyl Methacrylate Crosspolymer, Silica, Butylene Glycol, Nylon-12, Dimethicone/PEG-10/15 Crosspolymer, Alumina, Disteardimonium Hectorite, Ethylene Brassylate, Hydrogen Dimethicone, Hydrolyzed Vegetable Protein, Laureth-7, Magnesium Sulfate, Methicone, Mica, Polyglyceryl-3 Diisostearate, Salicylic Acid, Sodium Hyaluronate, Tetrasodium EDTA, Tocopheryl Acetate, Tribehenin, Triethoxycaprylylsilane, Triethyl Citrate, Ethylparaben, Methylparaben, Phenoxyethanol.

MAY CONTAIN:

[Iron Oxides (CI 77491), Iron Oxides (CI 77492), Iron Oxides (CI 77499), Titanium Dioxide (CI 77891)] B02217

Purpose

Sunscreen

To Use

Shake well. Apply to one area at a time, blending quickly. Remove with facial cleanser.

DOSAGE AND ADMINISTRATION

Apply liberally 15 minutes before sun exposure.

KEEP OUT OF REACH OF CHILDREN

Keep out of the reach of children. If product is swallowed, get medical help or contact a Poison Control Center right away.

Front and Back Label_Revlon Colorstay Normal to Dry Foundation

Front and Back Label_ Colorstay Normal to Dry Foundation

SPF 20